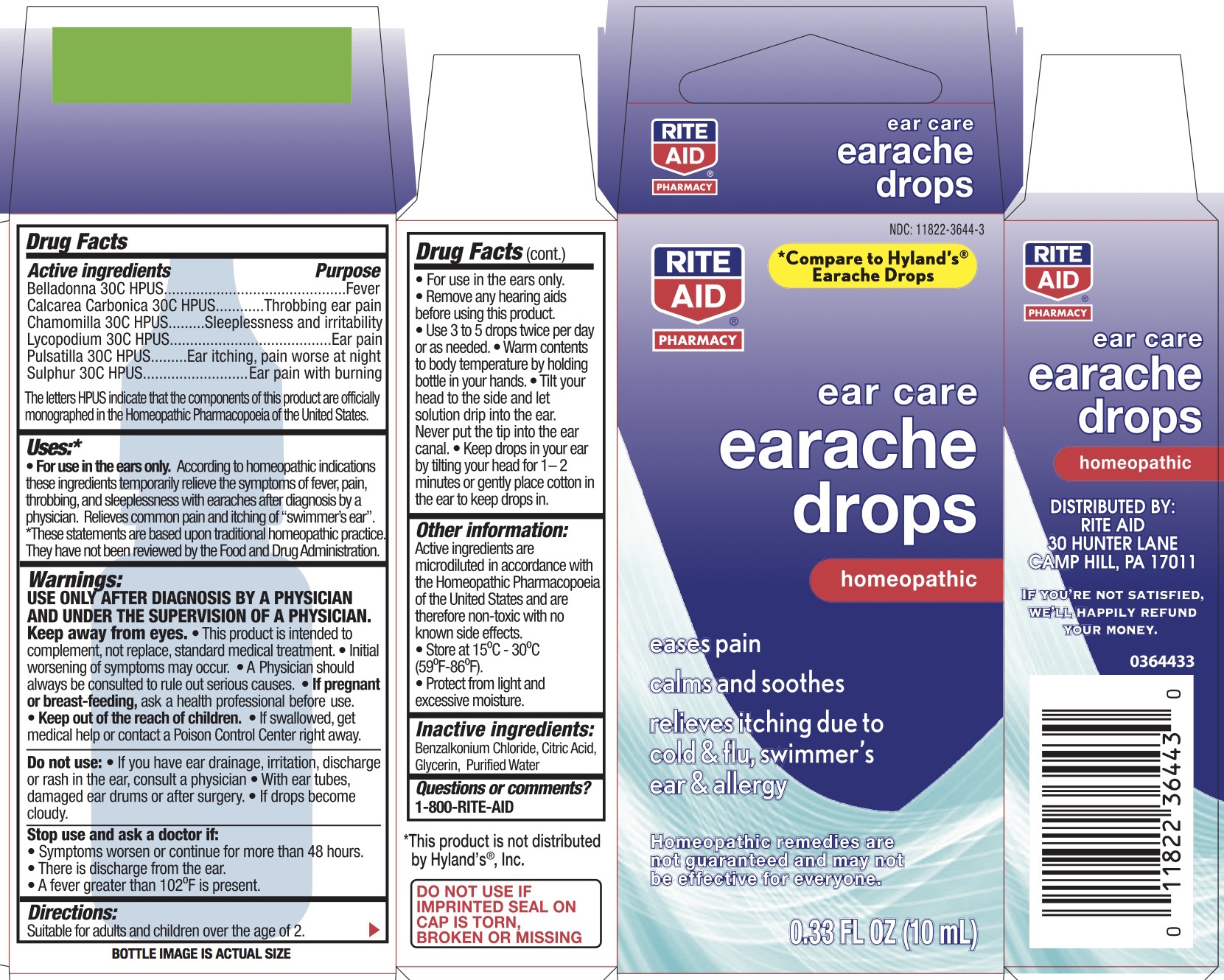 DRUG LABEL: EAR CARE EARACHE DROPS
NDC: 11822-3644 | Form: LIQUID
Manufacturer: Rite Aid Corporation
Category: homeopathic | Type: HUMAN OTC DRUG LABEL
Date: 20180316

ACTIVE INGREDIENTS: ATROPA BELLADONNA 30 [hp_C]/1 mL; OYSTER SHELL CALCIUM CARBONATE, CRUDE 30 [hp_C]/1 mL; MATRICARIA CHAMOMILLA 30 [hp_C]/1 mL; LYCOPODIUM CLAVATUM SPORE 30 [hp_C]/1 mL; ANEMONE PULSATILLA 30 [hp_C]/1 mL; SULFUR 30 [hp_C]/1 mL
INACTIVE INGREDIENTS: CITRIC ACID MONOHYDRATE; WATER; BENZALKONIUM CHLORIDE; GLYCERIN

EAR CARE EARACHE DROPS

Drug Facts

ACTIVE INGREDIENT

Active ingredients | Purpose
Belladonna 30C HPUS | Fever
Calcarea Carbonica 30C HPUS | Throbbing ear pain
Chamomilla 30C HPUS | Sleeplessness and irritability
Lycopodium 30C HPUS | Ear pain
Pulsatilla 30C HPUS | Ear itching, pain worse at night
Sulphur 30C HPUS | Ear pain with burning
"HPUS" indicates the components of this product are officially monographed in the Homeopathic Pharmacopœia of the United States.

Uses*

• For use in the ears only. According to homeopathic indications these ingredients temporarily relieve the symptoms of fever, pain, throbbing, and sleeplessness with earaches after diagnosis by a physician. Relieves common pain and itching of “swimmers ear”. *These statements are based upon traditional homeopathic practice. They have not been reviewed by the Food and Drug Administration.

Warnings

USE ONLY AFTER DIAGNOSIS BY A PHYSICIAN AND UNDER THE SUPERVISION OF A PHYSICIAN. Keep away from eyes. This product is intended to complement, not replace, standard medical treatment. Initial worsening of symptoms may occur. A physician should always be consulted to rule out serious causes.

PREGNANCY OR BREAST FEEDING

If pregnant or breast feeding, ask a health professional before use.

Stop and ask a doctor it:

- Symptoms worsen or continue for more than 48 hours
- There is discharge from the ear.
- A fever of greater than 102° is present

KEEP OUT OF REACH OF CHILDREN

Keep out of the reach of children. If swallowed, get medical help or contact a Poison Control Center right away.

Do not use: if you have ear drainage, irritation, discharge, or rash in the ear, consult a physician. With ear tubes, with damaged ear drums or after surgery. if drops become cloudy.

Directions

Suitable for adults and children over the age of 2.

• For use in the ears only

• Remove any hearing aids

• Use 3-5 drops twice per day or as needed. Warm contents to body temperature by holding bottle in your hands. Tilt ear upward for at least 2 minutes after application or gently place cotton in ear to keep drops in. Tilt your head to the side and let solution drip into the ear. Never put the tip in the ear canal. Keep drops in your ear by tilting your head for 1-2 minutes or gently place cotton in the ear to keep drops in.

Inactive ingredients

Benzalkonium Chloride, Citric Acid, Glycerine, Purified Water

Questions or comments?

(800) RITE-AID

(800-748-3243)

Other Information:

Active ingredients are microdiluted in accordance with the Homeopathic Pharmacopeia of the United States and are therefore non-toxic with no known side effects.

STORAGE AND HANDLING

• Store at 15°C-30°C (59°F-86°F)
• Protect from light and excessive moisture

PRINCIPAL DISPLAY PANEL - 10 mL Bottle Carton

NDC 11822-3644-3

ear care

earache drops

homeopathic

eases pain

calms and soothes

relieves itching due to

cold & flu, swimmers

ear & allergy

0.33 FL. OZ. (10 mL)